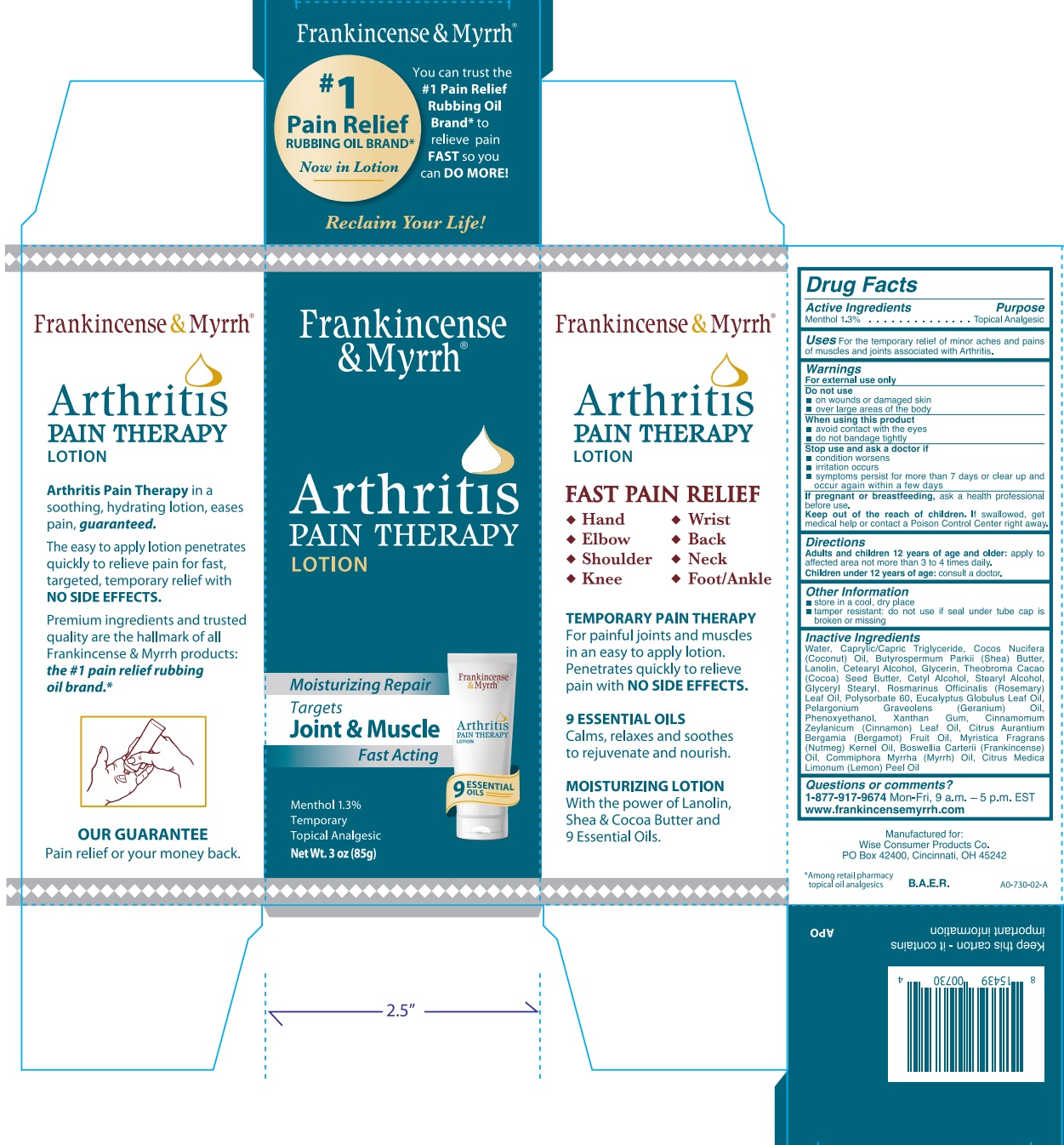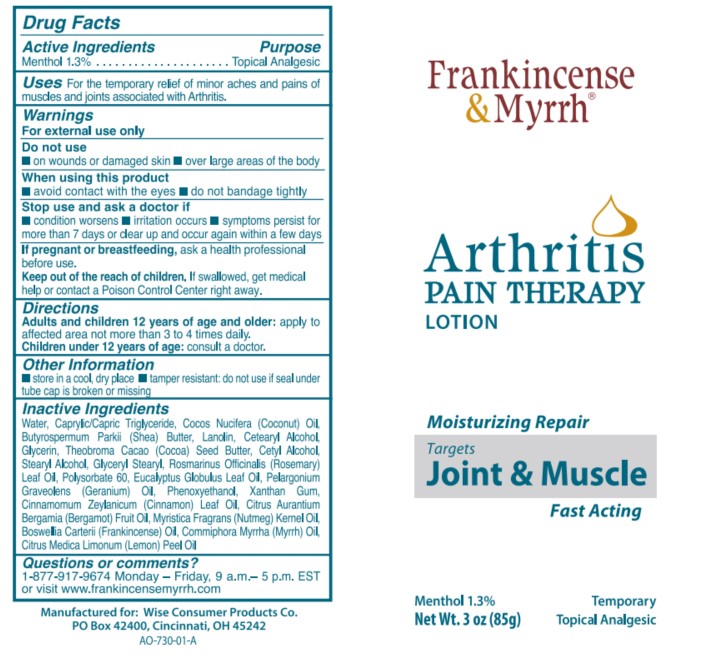 DRUG LABEL: Frankincense and Myrrh Arthritis Pain Therapy
NDC: 42346-731 | Form: LOTION
Manufacturer: Wise Consumer Products
Category: otc | Type: HUMAN OTC DRUG LABEL
Date: 20251217

ACTIVE INGREDIENTS: MENTHOL 1.3 g/100 g
INACTIVE INGREDIENTS: GLYCERYL MONOSTEARATE; WATER; MYRRH OIL; FRANKINCENSE OIL; LEMON OIL, COLD PRESSED; COCONUT OIL; NUTMEG OIL; COCOA BUTTER; CETOSTEARYL ALCOHOL; EUCALYPTUS OIL; SHEA BUTTER; LANOLIN; GERANIUM OIL, ALGERIAN TYPE; CETYL ALCOHOL; GLYCERIN; ROSEMARY OIL; POLYSORBATE 60; PHENOXYETHANOL; BERGAMOT OIL; MEDIUM-CHAIN TRIGLYCERIDES; STEARYL ALCOHOL; XANTHAN GUM; CINNAMON LEAF OIL

Frankincense & Myrrh Arthritis Pain Therapy Lotion

Active Ingredient

Menthol 1.3%

Purpose

Menthol 1.3%............................Topical Analgesic

Uses

For the temporary relief of minor aches and pains of muscles and joints associted with Arthritis.

Warnings

For external use only

Do not use

- on woulds or damaged skin
- over large areas of the body

When using this product

- avoid contact with the eyes
- do not bandage tightly

Stop use and ask a doctor if

- condition worsens
- irritation occurs
- symptoms persist for more than 7 days or clear up and occur again within a few days

PREGNANCY OR BREAST FEEDING

If pregnant or breastfeeding, ask a health professional before use.

KEEP OUT OF REACH OF CHILDREN

Keep out of the reach of children. If swallowed, get medical help or contact a Poison Control Center right away.

Directions

Adults and children 12 years of age and older: apply to affected area no more than 3 to 4 times daily.

Children under 12 years of age: consult a doctor.

Other Information

- store in a cool, dry place
- tamper resistant: do not use if seal under tube cap is broken or missing

Inactive Ingredients

Water, Caprylic/Capric Triglyceride, Cocos Nucifera (Coconut) Oil, Butyrospermum Parkii (Shea) Butter, Lanolin, Cetearyl Alcohol, Glycerin, Theobroma Cacao (Cocoa) Seed Butter, Cetyl Alcohol, Stearyl Alcohol, Glyceryl Stearyl, Rosmarinus Officinalis (Rosemary) Lear Oil, Polysorbate 60, Eucalyptus Globulus Leaf Oil, Pelargonium Graveolens (Geranium) Oil, Phenoxyethanol, Xanthan Gum, Cinnamomum Zeylanicum (Cinnamon) Leaf Oil, Citrus Aurantium Bergamia (Bergamot) Fruit Oil, Myristica Fragrans (Nutmeg) Kernel Oil, Boswellia Carterii (Frankincense) Oil, Commuphora Myrrha (Myrrh) Oil, Citrus Medica Limonum (Lemon) Peel Oil

Questions or comments?

1-877-917-9674 Mon-Fri, 9 a.m. - 5 p.m. EST

www.frankincensemyrrh.com

PACKAGE LABEL

Frankincense & Myrrh

Arthritis

Pain Therapy

Lotion

Moisturizing Repair

Targets

Joint & Muscle

Fast Acting

Menthol 1.3%

Temporary

Topical Analgesic

Net Wt. 3 oz (85g)